DRUG LABEL: Standardized Mite, Dermatophagoides pteronyssinus
NDC: 49288-0172 | Form: INJECTION, SOLUTION
Manufacturer: Antigen Laboratories, Inc.
Category: prescription | Type: HUMAN PRESCRIPTION DRUG LABEL
Date: 20090901

ACTIVE INGREDIENTS: Dermatophagoides pteronyssinus 10000 [AU]/1 mL
INACTIVE INGREDIENTS: Glycerin 0.525 mL/1 mL; Water; Sodium Chloride 0.0095 g/1 mL; Sodium Bicarbonate 0.0024 g/1 mL

Allergenic Extract

WARNINGS
Standardized allergenic extract is intended for use by physicians who are experienced in the administration of standardized (AU/ml) allergenic extracts for immunotherapy and the emergency care of anaphylaxis, or for use under the guidance of an allergy specialist. Standardized allergenic extracts are not directly interchangeable with other allergenic extracts. The initial dose must be based on skin testing as described in the "DOSAGE AND ADMINISTRATION" section of this insert. Patients being switched from other types of extract to standardized allergenic extracts should be started as though they were coming under treatment for the first time. Patients should be instructed to recognize adverse reaction symptoms and cautioned to contact the physician's office if reaction symptoms occur. As with all allergenic extracts, severe systemic reactions may occur. In certain individuals, these life-threatening reactions may result in death. Patients should be observed for at least 20 minutes following treatment and emergency measures, as well as personnel trained in their use, should be immediately available in the event of a life-threatening reaction. Patients being switched from one lot of extract to another from the same manufacturer should have the dose reduced by 75%.
This product should not be injected intravenously. Deep subcutaneous routes have proven to be safe, see "WARNINGS", "PRECAUTIONS", "ADVERSE REACTIONS" and "OVERDOSAGE" sections.
Sensitive patients may experience severe anaphylactic reactions resulting in respiratory obstruction, shock, coma and/or death.
Patients receiving beta-blockers may not be responsive to epinephrine or inhaled bronchodilators. Respiratory obstruction not responding to parenteral or inhaled bronchodilators may require theophylline, oxygen, intubation and the use of life support systems. Parenteral fluid and/or plasma expanders may be utilized for treatment of shock. Adrenocorticosteroids may be administered parenterally or intravenously. Refer to "WARNINGS", "PRECAUTIONS", and "ADVERSE REACTIONS" sections.

DESCRIPTION
The extract is sterile and intended for dilution prior to skin testing and/or immunotherapy. The routes of administration for diagnostic purposes are intradermal or prick-puncture of the skin. The route of administration for immunotherapy is subcutaneous. The designation AU/ml (Allergy Units per ml) is unitage based upon the relative potency of this standardized mite extract when compared by ELISA competition to the F.D.A. Mite Allergenic Reference Standard labeled 10,000 AU/ml assigned on the basis of quantitative skin testing by the ID50EAL Method.^1,2,3,4,5,16 Lower concentrations (e.g. 5,000 AU/ml and 3,000 AU/ml) are prepared by dilution of stock concentrates. Mite mixtures containing equal volumes of D. farinae and D. pteronyssinus are available at 5,000 AU/ml, 2,500 AU/ml and 1,500 AU/ml.
Active allergens are described by common and scientific name on the stock concentrate container label.
INGREDIENTS: Extract of Standardized Mites contain at least 99.0% adult mites and mite stages. This product may contain trace amounts of yeast and/or pork products; sodium chloride 0.95%; sodium bicarbonate 0.24%; 50% v/v glycerine as stabilizing agent and preservative.
Following is a brief description of the standardized quality procedures applied to these extracts:
1. The source material is carefully selected from whole body adult mites and mite stages cultured from a medium containing no material of human origin. The source material is extracted with a saline buffer and 50% v/v glycerine.
2. Several manufacturers submitted intradermal skin test data on Biopol Laboratories mite medium extract using patients who were puncture test positive (erythema greater than 40 mm) to either D. farinae or D. pteronyssinus extracts. By intradermal testing, there was 1 positive (erythema greater than 20 mm) in 44 individuals at an estimated 1% level of medium contamination of mites, and 4 positives in 40 individuals at an estimated 10% contamination. Two of the individuals who were skin test positive to the mite extract and who were also skin test positive to the mite medium extract were also skin tested by the puncture method with an extract of yeast (Saccharomyces sp.) and were positive.
3. A ninhydrin protein analysis is completed to compare with the standard extract.
4. Each lot is standardized against the F.D.A. reference standard extract for total biologic activity by means of ELISA competition.
5. The standardized mite extract is analyzed for glycerine content to insure a minimum of 50% v/v glycerine for optimal stability during the entire dating period.

CLINICAL PHARMACOLOGY
As a consequence of the discovery of IgE and the development of methods to identify and quantify antiallergen IgE levels, interest in recent years has centered around the utilization of in vivo and in vitro diagnostic procedures. ^3,5
The mode of action of immunotherapy with allergenic extracts is still under investigation. Subcutaneous injections of increasing doses of Standardized Mite allergenic extract into patients with allergic disease have been shown to result in both humoral and cellular changes including the production of allergen-specific IgG antibodies, the suppression of histamine release from target cells, decrease in circulating levels of antigen specific IgE antibody over long periods of time and suppression of peripheral blood T-Iymphocyte cell responses to antigen.^10,14,15

INDICATIONS AND USAGE
Standardized Mite allergenic extract is indicated for diagnostic testing and for the treatment (immunotherapy) of patients whose histories indicate that upon natural exposure to the allergen, they experience allergic symptoms. Confirmation is determined by skin testing. An orderly approach to the diagnostic use of allergenic extracts usually begins with direct skin testing. This product is not intended for treatment of patients who do not manifest immediate hypersensitivity reactions to the allergenic extract following skin testing.
Mite mixtures should not be used for diagnostic skin testing. The individual mites should be used. Mite mixtures may be used for immunotherapy to treat patients who demonstrated sensitivity to both D. farinae and D. pteronyssinus mites. Patients who react to both D. farinae and D. pteronyssinus have demonstrated a significant cross-reactivity. Caution should be used in escalating treatment with mite mixtures.^21
PRICK-PUNCTURE TESTING: A positive control using Histamine Phosphate is important to identify those patients whose skin may not be reactive due to medications, metabolic or other reasons. A diluent control, if negative, would exclude false-positive reactions due to ingredients in the diluent or patients who have dermatographism.
To identify highly sensitive individuals and as a safety precaution, it is recommended that prick-puncture test using a drop of the extract concentrate (10,000 AU/ml) be performed prior to initiating very dilute intradermal testing. Prick-puncture testing is performed by placing a drop of extract concentrate on the skin and puncturing the skin through the drop with a small needle such as a bifurcated vaccinating needle. The most satisfactory sites on the back for skin testing are from the posterior axillary fold to 2.5 cm from the spinal column, and from the top of the scapula to the lower rib margins. The best areas on the arms are the volar surfaces from the axilla to 2.5 or 5 cm above the wrist, skipping the anticubital space. Glycerinated Mite extracts containing 10,000 AU/ml are recommended for prick-puncture testing. Skin reactions are based on size of erythema and wheal. For interpretation of skin reactions, refer to chart below.

GRADE | mm ERYTHEMA | mm WHEAL
0 | less than 5 | less than 5
+/- | 5-10 | 5-10
1+ | 11-20 | 5-10
2+ | 20-30 | 5-10
3+ | 31-40 | 10-15 or with pseudopods
4+ | greater than 40 | greater than 15 or with many pseudopods

Smaller, less conclusive reactions may be considered positive in conjunction with a definitive history of symptoms on exposure to the mite allergen. The more sensitive the patient the higher the probability that he/she will have symptoms related to the exposure of the offending allergen. Hence, the importance of a good patient history. Less sensitive individuals can be tested intradermally with an appropriately diluted extract.
A clinical study using the same patients with positive prick-puncture test (10) using the ID50EAL Method, Intradermal Dilution for 50 mm Sum of Erythema D50 Determines the Allergy Unit, has demonstrated the following:
Skin test by prick-puncture test using Standardized D. farinae Mite, 10,000 AU/ml was performed in 10 patients. The mean sum of erythema diameter was 76.6 mm (Range 45-104 mm). Skin test by prick-puncture test using Standardized D. pteronyssinus Mite, 10,000 AU/ml in 10 patients, the mean sum of erythema diameter was 74.7 mm (Range 43-109 mm).

TABLE 1
STANDARDIZED MITE ALLERGENIC EXTRACTS
LABELED 10,000 AU/ml

10,000 AU/ml 1:3 Dilutions | 10,000 AU/ml 1:5 Dilutions | 10,000 AU/ml 1:10 Dilutions
*C 10,000 3^-1 3,333 3^-2 1,111 3^-3 370.37 3^-4 123.45 3^-5 41.15 3^-6 13.71 3^-7 4.57 3^-8 1.52 3^-9 0.508 3^-10 0.169 3^-11 0.056 3^-12 0.018 3^-13 0.0063 3^-14 0.0021 3^-15 0.0007 | *C 10,000 5^-1 2,000 5^-2 400 5^-3 80 5^-4 16 5^-5 3.20 5^-6 0.64 5^-7 0.128 5^-8 0.0256 5^-9 0.00512 5^-10 0.00102 | *C 10,000 10^-1 1,000 10^-2 100 10^-3 10 10^-4 1 10^-5 0.10 10^-6 0.01 10^-7 0.001 10^-8 0.0001 10^-9 0.00001

*C = Concentration

SINGLE DILUTION INTRADERMAL TESTING: The surface of the upper and lower arm is the usual location for skin testing. It is important that a new, sterile, disposable syringe and needle be used for each extract tested. Intracutaneous test dilutions should be made with aqueous diluent. (1) Start testing with the most dilute allergenic extract concentration. (2) A volume of 0.02-0.05 ml should be injected slowly into the superficial skin layers making a small bleb (superficial wheal). (3) For patients without a history of extreme sensitivity, a prick-puncture test of less than 2+, the initial dilution for skin testing should contain 0.02 to 0.06 AU/ml (see Table I). For very sensitive patients with a prick-puncture of greater than 2+, a further dilution should be made to 0.002 to 0.006 AU/ml (see Table I). If after 20 minutes no skin reaction is obtained, continue the testing using five-fold or ten-fold increments in potency until a reaction of 1+ or until the concentration of 2,000 AU (five-fold) or 1,000 AU (ten-fold) has been tested with a glycerine control. Glycerine may be used at a dilution of 0.5% as long as 0.5% glycerine produces negative control. The diluent should be tested and included in the interpretation of the skin reactions.^16
INTRADERMAL TESTING–SKIN ENDPOINT TITRATION: The allergenic extracts to which the patient is sensitive, the patient's degree of sensitivity and the dose of allergen to be used in immunotherapy can be determined through the use of intracutaneous skin tests involving progressive five-fold dilutions of allergenic extracts, prepared and refrigerated at 2-8° C. The critical variable is the size if the wheal and erythema produced by the intracutaneous injection of 0.01 to 0.02 ml of the test allergen producing a 4 mm diameter superficial skin wheal. For patients demonstrating a prick-puncture skin test of less than 2+, an initial screening dilution of 0.02-0.06 AU/ml is safe (see Table I). For patients demonstrating a prick-puncture skin test greater than 2+, an initial screening dilution of 0.002 to 0.006 AU/ml is safe. The skin endpoint is detected by noting the dilution that produces a wheal 2 mm larger than non-reacting dilutions (5 mm negative wheal) until progressive whealing with each five-fold increase in test potency occurs, i.e., a 5 mm (negative), 7 mm, 9 mm, 11 mm is the normal sequence of whealing. The 7 mm wheal would be the endpoint. The endpoint dilution is used as an initial dose concentration for immunotherapy. An endpoint dose of 0.15 ml is a safe initial dose to be followed by escalation to the optimal maximum tolerated dose for each individual.
Using Standardized D. farinae Mite, 10,000 AU/ml on 10 patients, the mean AU for 50 mm sum of erythema was 0.02 AU (Standard deviation was 1.4). Using Standardized D. pteronyssinus Mite 10,000 AU/ml in 10 patients, the mean AU for 50 mm sum of erythema was 0.02 AU (Standard deviation was 1.7).

CONTRAINDICATIONS
Do not administer in the presence of diseases characterized by bleeding diathesis. Individuals with autoimmune disease may be at risk of exacerbating symptoms of the underlying disease, possibly due to routine immunization. Patients who have experienced a recent myocardial infarction may not be tolerant of immunotherapy. Children with nephrotic syndrome probably should not receive injections due to a variety of seemingly unrelated events, such as immunization causing exacerbation of their nephrotic disease.

WARNINGS
Extreme caution is necessary when using diagnostic skin tests or injection treatment in highly sensitive patients, who have experienced severe symptoms or anaphylaxis by natural exposure or previous skin testing or treatment. IN THESE CASES BOTH THE POTENCY FOR SKIN TESTS AND THE ESCALATION OF THE TREATMENT DOSE MUST BE ADJUSTED TO THE PATIENT'S SENSITIVITY TOLERANCE. Refer to boxed “WARNINGS" and "OVERDOSAGE" section.
Epinephrine 1:1000 should be available. When changing immunotherapy from an unstandardized to an AU/ml standardized allergenic extract, dose adjustment, if indicated, should be based on such considerations as the results of skin endpoint titration (see "INDICATIONS AND USAGE" section). Patient re-evaluation may be necessary. Injections should never be given intravenously. A 5/8 inch, 25 gauge needle on a sterile syringe will allow deep subcutaneous injection. Precaution of withdrawing the plunger slightly after inserting the needle is advisable to determine if a blood vessel has been entered. DO NOT INJECT INTRAVENOUSLY. Proper measurement of the dose and caution in making the injection will minimize reactions. Patients should be detained for twenty to thirty minutes after injection and advised to notify the office immediately if symptoms or reactions occur.
Patients being switched from one lot of extract to another from the same manufacturer should have the dose reduced to 75%. Also, this extract should be temporarily withheld or dosage reduced in the following conditions: 1) flu or other infection with fever; 2) exposure to excessive amounts of allergen prior to injection; 3) rhinitis and/or asthma exhibiting severe symptoms.

PRECAUTIONS
General:
Immunotherapy must be given under physician's supervision. Sterile solutions, vials, syringes, etc. must be used. Aseptic technique should be observed in making dilutions, skin testing and extracts for treatment. The usual precautions in administering allergenic extracts are necessary. Disposable, sterile syringe and needle should be used for each individual patient to prevent transmission of serum hepatitis, HIV and other infectious agents from one person to another. The current standard method of immunotherapy dates back to the earliest studies by Noon. Therapy is begun with a low dose which has been shown to be tolerated by both experience and skin testing. The initial dilution of allergenic extract, starting dose, and progression of dosage must be carefully determined on the basis of the patient's history and results of skin tests. Patients with a history of severe sensitivity and markedly positive skin tests in high dilutions of the allergenic extract should be started with low doses of highly diluted extract. Pregnancy or a history of prior reactions to allergen immunotherapy dictates the need to start with small quantities of antigen.
It cannot be overemphasized that, under certain unpredictable combinations of circumstances, anaphylactic shock is always a possibility. Other possible systemic reaction symptoms are, in varying degrees of severity, fainting, pallor, bradycardia, hypotension, angioedema, cough, wheezing, conjunctivitis, rhinitis, and urticaria.^13,14
With careful attention to dosage and administration, such reactions occur infrequently, but it must be remembered that allergenic extracts are highly potent to sensitive individuals and OVERDOSE could result in anaphylactic symptoms. Therefore, it is imperative that physicians administering allergenic extracts understand and be prepared for the treatment of severe reactions.
Refer to "OVERDOSAGE" section for description of treatment for anaphylactic reactions.
Information for Patients:
Patient should remain under observation of a nurse, physician, or personnel trained in emergency measures for at least 20 minutes following injection of immunotherapy. Any adverse reactions during or after leaving office should be reported to the physician or his qualified personnel.
Carcinogenicity, Mutagenicity, Impairment of Fertility:
Long term animal studies have not been conducted with allergenic extracts to determine their potential for carcinogenicity, mutagenicity or fertility impairment.
Pregnancy Category C:
Animal reproduction studies have not been conducted with allergenic extracts. It is not known whether allergenic extracts cause fetal harm during pregnancy or affect reproductive capacity. A systemic reaction to allergenic extracts could cause uterine contractions leading to spontaneous abortion or premature labor. Allergenic extracts should be used during pregnancy only if potential benefit justifies potential risk to fetus.^11
Nursing Mothers:
It is not known whether allergenic extracts are excreted in human milk. Because many drugs are excreted in human milk, caution should be exercised when allergenic extracts are administered to a nursing woman.
Pediatric Use:
Although standardized mite extract has not been studied in children, allergenic extracts (including mite) have been used in children with no evidence of special problems related to safety or other specific hazards.^17,18,19,20,21,22
Drug Interactions:
Antihistamines. The H1 antagonists which block the capillary effects of histamine, inhibit the wheal-and-flare reaction. Moreover, H1 antagonists reduce the wheal reaction induced by mast cell secretagogues or allergens in sensitized patients. The most potent H1 antagonists seems to be astemizole, which blocks the wheal and flare induced by histamine for a long period of time, ranging from a few days to 40 days. Although a large interpatient variation exists, hydroxyzine and clemastine seem to be more potent inhibitors than chlorpheniramine, and promethazine. On the other hand, tripelennamine, diphenhydramine, cyproheptadine, and perphenazine induce a variable, but rather low, degree of inhibition.^23 The duration of the inhibitory effect varies from 1 day to up to 10 days, according to the drug and the patient's sensitivity. Hydroxyzine and clemastine usually exhibit a longer blockade. Sustained-release H1 antagonists may produce a longer inhibitory effect. Long-term treatment with antihistamines may reduce the inhibitory effects of these drugs on skin tests. Long et al. noticed that after 3 weeks of treatment with hydroxyzine, its suppressive effect, as well as that induced by other H1 blockers, was significantly reduced. These data indicate that the 24-hour period without antihistamine sometimes recommended prior to skin testing may not be sufficient for reliable testing. If the histamine control is normal, it suggests that accurate testing can be performed, because the reactions to histamine and allergen were found to be equally suppressed by hydroxyzine. ^23
Tricyclic antidepressants exert a potent and sustained decrease of skin reactions to histamine. This effect may last for a few weeks. Tranquilizers and antiemetic agents of the phenothiazine class have H1 antihistaminic activity and can block skin tests.^23
Corticosteroids. Short-term (less than 1 week) administration of corticosteroids at the therapeutic doses used in asthmatic patients does not modify the cutaneous reactivity to histamine, compound 48/80, or allergen. Long-term corticosteroid therapy modifies the skin texture and makes the interpretation of immediate skin tests more difficult.^23
Theophylline. It appears that theophylline need not be stopped prior to skin testing. ^23
Beta-adrenergic agents. Inhaled beta2 agonists in the usual doses used for the treatment of asthma do not usually inhibit allergen-induced skin tests. However, oral terbutaline and parenteral ephedrine were shown to decrease the allergen-induced wheal. Such an effect seems to be related to the antianaphylactic properties of beta2 agonists and, to a lesser extent, to a direct action on the dermal vasculature. Conversely, beta-blocking agents such as Propanolol can significantly increase skin reactivity. ^23
Cromolyn. Cromolyn inhaled or injected prior to skin tests with allergens or degranulating agents does not alter the skin whealing response. ^23
Other drugs. Other drugs have been shown to decrease skin test reactivity. Among them, dopamine is the best-documented compound. ^23
Specific Immunotherapy. A decreased skin test reactivity has been noticed by many authors for patients undergoing specific immunotherapy with pollen extracts, grass pollen allergoids, mites, or hymenoptera venoms, or in professional beekeepers who are spontaneously desensitized. Finally, it was shown that specific immunotherapy in patients treated with ragweed pollen extract induced a decreased late-phase reaction. ^23

ADVERSE REACTIONS
Adverse reactions include, but are not necessarily limited to urticaria; itching; edema of extremities; respiratory wheezing or asthma; dyspnea; cyanosis; tachycardia; lacrimation; marked perspiration; flushing of face, neck or upper chest; mild persistent clearing of throat; hacking cough or persistent sneezing.
1) Local Reactions
Small amounts of erythema and swelling at the site of injection are common, the extent varying with the patient. Such reactions should not be considered significant unless they persist for at least 24 hours or exceed 50 mm in diameter.
Larger local reactions are not only uncomfortable, but indicate the possibility of a systemic reaction if dosage is increased. In such cases, the dosage should be reduced to the last level not causing the reaction and maintained at this level for two or three treatments before cautiously increasing again.
Large, persistent local reactions or minor exacerbations of the patient's allergic symptoms may be treated by local cold applications and/or use of oral antihistamines, but they should be considered a warning of possible severe systemic reactions and the need for temporarily reduced dosages.
A mild burning immediately after the injection is to be expected; this usually leaves in 10-20 seconds. Prolonged pain is usually the result of intramuscular injection, making this injection route undesirable. Subcutaneous injection is the recommended route.
2) Systemic Reactions
Systemic reactions range from mild exaggeration of patient's allergic symptoms to anaphylactic reactions. Very sensitive patients may show a rapid response. In some instances, a severe systemic reaction with blood pressure fall and/or shock may occur. Quantitation of patient's sensitivity combined with careful early observation is essential for safe skin testing and treatment.
Reports from regulatory authorities in Sweden to the F.D.A. indicated that several deaths have been associated with the use of mite extracts. The F.D.A. was subsequently informed that these deaths may have been related to use by physicians untrained in the administration of potent extracts rather than a product defect. It should be noted that anaphylaxis and deaths following the injection of mite and other extracts have also been reported by the British Committee on Safety in Medicine in the British Medical Journal, Vol. 293, p. 948, 1986.^24
Patients receiving beta-blockers may not be responsive to epinephrine or inhaled bronchodilators. The following are commonly prescribed beta-blockers: Levatol, Lopressor, Propanolol Intersol, Propanolol HCL, Blocadren, Propanolol, Inderal-LA, Visken, Corgard, Ipran, Tenormin, Timoptic. Ophthalmic beta-blockers: Betaxolol, Levobunolol, Timolol, Timoptic. Chemicals that are beta-blockers and may be components of other drugs: Acebutolol, Atenolol, Esmolol, Metoprolol, Nadolol, Penbutolol, Pindolol, Propanolol, Timolol, Labetalol, Carteolol.

OVERDOSAGE
If a systemic or anaphylactic reaction does occur, the first treatment should be injection intramuscularly or subcutaneously 0.3 to 0.5 ml of 1:1000 epinephrine-hydrochloride into the opposite arm or gluteal area. Apply tourniquet above the site of allergenic extract injection and loosen briefly at 5 minute intervals to prevent circulatory impairment. If oxygen is indicated, it may be administered by nasal cannula or ambu bag.
The epinephrine HCL 1:1000 dose for infants to 2 years is 0.05 to 0.1 ml; for children 2 to 6 years it is 0.15 ml; for children 6 to 12 years it is 0.2 ml.
Studies on asthmatic subjects reveal that plasma concentrations of theophylline of 5 to 20 ug/ml are associated with therapeutic effects. Toxicity is particularly apparent at concentrations greater than 20 ug/ml. A loading dose of aminophylline of 5.6 mg/kg intravenously followed by 0.9 mg/kg per hour results in plasma concentrations of approximately 10 ug/ml (Mitenko and Ogilvie 1973b; Nicholson and Chick 1973).^4
Other beta-adrenergic drugs such as isoproterenol, isoetharine, or albuterol may be used by inhalation. The usual dose to relieve broncho-constriction in asthma is 0.5 ml or the 0.5% solution for isoproterenol HCL; albuterol is longer acting than isoproterenol by any route of administration. The albuterol inhaler delivers approximately 90 mcg of albuterol from the mouthpiece. The usual dosage for adults and children would be two inhalations repeated every 4 to 6 hours. Isoetharine supplied in the Bronkometer unit delivers approximately 340 mcg isoetharine. The average adult dose is one to two inhalations.
Patients who have been taking a beta-blocker may be unresponsive to epinephrine. Epinephrine or beta-adrenergic drugs (Alupent) may be ineffective. These drugs should be administered even though a beta-blocker may have been taken. The following treatment will be effective whether or not patient is taking a beta-blocker: Aminophylline IV, slow push or drip, Atrovent (Ipratropium bromide) Inhaler, 3 inhalations repeated, Atropine, 0.4 mg/ml, 0.75 to 1.5 ml lM or IV, Solu-Cortef, 100-200 mg IM or IV, Solu-Medrol, 125 mg IM or IV, Glucagon, 0.5-1 mg IM or IV, Benadryl, 50 mg IM or IV, Cimetidine, 300 mg IM or IV, Oxygen via ambu bag.

DOSAGE AND ADMINISTRATION
Parenteral drug products should be inspected visually for particulate matter and discoloration prior to administration, whenever solution and container permit.
Normally, immunotherapy with standardized mite allergenic extracts can be started with 0.15 ml of the endpoint of reaction.
If the first injection of the initial dilution of extract is tolerated without significant local reaction, increasing doses by 5-20% increments of that dilution may be administered. The rate of increase in dosage in the early stages of treatment with highly diluted extracts is usually more rapid than the rate of increase possible with more concentrated extracts. This schedule is intended only as a guide and must be modified according to the reactivity of the individual patient. Needless to say, the physician must proceed cautiously in the treatment of the highly sensitive patient who develops large local or systemic reactions.
Some patients may tolerate larger doses of the standardized mite allergenic extract depending on patient response.^7 Because dilute extracts tend to lose activity on storage, the first dose from a more concentrated vial should be the same or less than the previous dose.^8,12
The physician who undertakes immunotherapy should be concerned with the degree of sensitivity of the patient. See "INDICATIONS AND USAGE" section. Strongly positive skin tests may be risk factors for systemic reactions. Less aggressive immunotherapy schedules may be indicated for such patients. Maintenance dose potency must be established by the physician's clinical observation and experience.^6,13
Serial five-fold or ten-fold dilutions of the extract are used to make more dilute extract concentrations. Other concentrations can be prepared by appropriate dilutions. In brief, the allergist can prepare any dilution of extract that is considered appropriate for the patient.
Dosages progressively increase thereafter according to the tolerance of the patient at intervals of one to seven days until, (1) the patient achieves relief of symptoms, (2) induration at site of injection is no larger than 50 mm in 36 to 48 hours, (3) a maintenance dose, the largest dose tolerated by the patient short of aggravating existing symptoms, systemic symptoms, or anaphylaxis, or demonstrates untoward reactions that indicate the dose to be excessive. This maintenance dose may be continued at regular intervals perennially. It may be necessary to adjust the progression of dosage downward to avoid local and constitutional reactions.

HOW SUPPLIED
The concentrate of standardized mite allergenic extract is expressed in AU/ml. It is supplied in 10,000, 5,000 and 3,000 AU/ml. The mite extract is available in 10 ml, 30 ml, and 50 ml containers. Extracts in dropper bottles are available for prick-puncture testing.
Mite mixtures for immunotherapy only containing equal volumes of Dermatophagoides farinae and Dermatophagoides pteronyssinus are available in the following potencies-5,000 AU/ml, 2,500 AU/ml, and 1,500 AU/ml.

STORAGE
Store all stock concentrates and dilutions at 2-8 degrees C. Keep at this temperature during office use. The expiration date of allergenic extracts containing 10,000 AU/ml is listed on the container label. Dilutions of 10,000 AU/ml concentrate containing less than 50% glycerol are less stable. If loss of potency is suspected, concentrate can be checked by skin testing with equal units of a freshly prepared dilution on known mite allergic individuals.

REFERENCES
1. Evans, R., Pence, H., Kaplan, H., Rocklin, R.: The effect of Immunotherapy on Humoral and Cellular Response in Ragweed Hay Fever. J. Clin. lnv. 57: 1378-1385, 1976.
2. Gleich, G.J., Yunginger, J.W.: The Radio Allergo Sorbent Test: A Method to Measure IgE Antibodies, IgG Blocking Antibodies, and the Potency of Allergy Extracts. Bull. N.Y. Acad. Sci. 57 (7): 559-567, 1981.
3. Allergenic Products: Antigen E. Potency Test: Additional Standards for Miscellaneous Products, 21 CFR Part 680, Federal Register, Vol. 46, No. 147, Friday, July 31, 1981, Rules and Regulations, pp. 39128-39136.
4. Goodman, L.S., Gillman, A.: Editors The Pharmacological Basis of Therapeutics, MacMillan Publishing Co., Inc., Chapter 19, p. 375.
5. Kniker, W.T.: "Clinical Science and Common Sense in the Diagnosis and Immunotherapy of Respiratory Allergy," Continuing Education for the Family Physician, Vol. 10, No. 5, May 1979, pp.16-33.
6. Matthews, K., et al: Rhinitis, Asthma and the Other Allergic Diseases, NIAID Task Force Report, U.S. Dept. HEW, NIH Publication No. 79-387, Chapter 4, pp. 213-217, May 1979.
7. Ishizaka, K.: Control of IgE Synthesis, Third Edition, Allergy Principles and Practices, C.V. Mosby Co.,Vol. l, Chap. 4, p. 52,1988.
8. Nelson, H.S.: "The Effect of Preservatives and Dilution on the Deterioration of Russian Thistle (Salsola pestifer), a pollen extract." The Journal of Allergy and Clinical Immunology. Vol. 63, No.6, pp. 417-425, June 1979.
9. Norman, P.S., Lichtenstein, L.M., Ishizaka, K.: "Diagnostic tools in ragweed hay fever. A comparison of direct skin tests IgE antibody measurements and basophil histamine release." The Journal of Allergy and Clinical lmmunology, Vol. 52, 1973, pg. 210.
10. Rocklin, R.E., Sheffer, A.L., Grainader, D.K. and Melmon, K.: "Generation of antigen-specific suppressor cells during allergy desensitization", New England Journal of Medicine, Vol. 302, pp. 1213-1219, May 29,1980.
11. Seebohm, P.M., et al: Panel on Review of Allergenic Extracts, Final Report, Food and Drug Administration, pp. 9-48, March 13, 1981.
12. Stevens, E.: Cutaneous Tests, Regulatory Control and Standardization of Allergenic Extracts, First lnternational Paul Ehrlich Seminar, Frankfurt, Germany, pp. 133-138, May 20-22, 1979.
13. Van Metre, T., Adkinson, N., Amodio, F., Lichtenstein, L., Mardinay, M., Norman, P., Rosenberg, G., Sobotka, A., Valentine, M.: "A Comparative Study of the Effectiveness of the Rinkel Method and the Current Standard Method of Immunology for Ragweed Pollen Hay Fever," The Journal of Clinical Allergy and Immunology, Vol. 66, No. 6, p. 511, December 1980.
14. Wasserman, S.: The Mast Cell and the Inflammatory Response. The Mast Cell–its role in health and disease. Proceedings of an International Symposium, Davos, Switzerland, Pitman Medical Publishing Co., pp. 9-20, 1979.
15. Perelmutter, L.: IgE Regulation During Immunotherapy of Allergic Diseases. Annals of Allergy, Vol. 57, August 1986.
16. Baer, H., Anderson, M.C., Turkeltaub, P.C.: Allergenic Extracts, Third Edition, Allergy Principles and Practice, C.V. Mosby Co., Vol. I, Chap. 17, p. 373, 1988.
17. Wasserman, S., Marquart, D.: Anaphylaxis, Third Edition, Allergy Principles and Practice, C.V. Mosby Co., Vol. 1, Chap. 58, pp. 1365-1376, 1988.
18. Solomon, W., Matthews, K.: Aerobiology and inhalant allergens, Third Edition, Allergy Principles and Practice, Vol. I, Chapt. 16, pg. 312, edited by Middleton et al.
19. Bullock, J., Frick, O.: Mite Sensitivity in House Dust Allergic Children, Am. J. Dis. Child., pp.123222, 1972.
20. Kawai, T., Marsh, D., Lichtenstein, L., Norman, P.: The Allergens Responsible for House Dust Allergy. I. Comparison of Dermatophagoides pteronyssinus and House Dust Extracts by Assay of Histamine Release from Allergic Human Leukocytes. J. Allergy Clin. Immunol. 50: 117, 1972.
21. Willoughby, J.W.: Inhalant Allergy Immunotherapy with Standardized and Nonstandardized Allergenic Extracts, American Academy of Otolaryngology-Head and Neck Surgery: Instructional Courses, C.V. Mosby Co., Vol. 1, Chapter 15, September 1988.
22. Allergy Principles and Practice,Third Edition, Vol. I and II, Edited by Middleton, Reed, Ellis, Adkinson, Yunginger, C.V. Mosby Co., 1988.
23. Allergy Principles and Practice, Third Edition, Vol. I, Chapt. 19, "In vivo methods for study of allergy: Skin tests", pg. 419-436, Middleton, Reed, Ellis, Adkinson, Yunginger, C.V. Mosby Co., 1988.
24. Reid, Michael J., Lockey, Richard F., Turkeltaub, Paul C., M.D., Platts-Mills, Thomas: "Survey of Fatalities from Skin Testing and Immunotherapy 1985-1989", Journal of Allergy and Clinical Immunology, Vol. 92, No. 1, pp. 6-15, 1993.